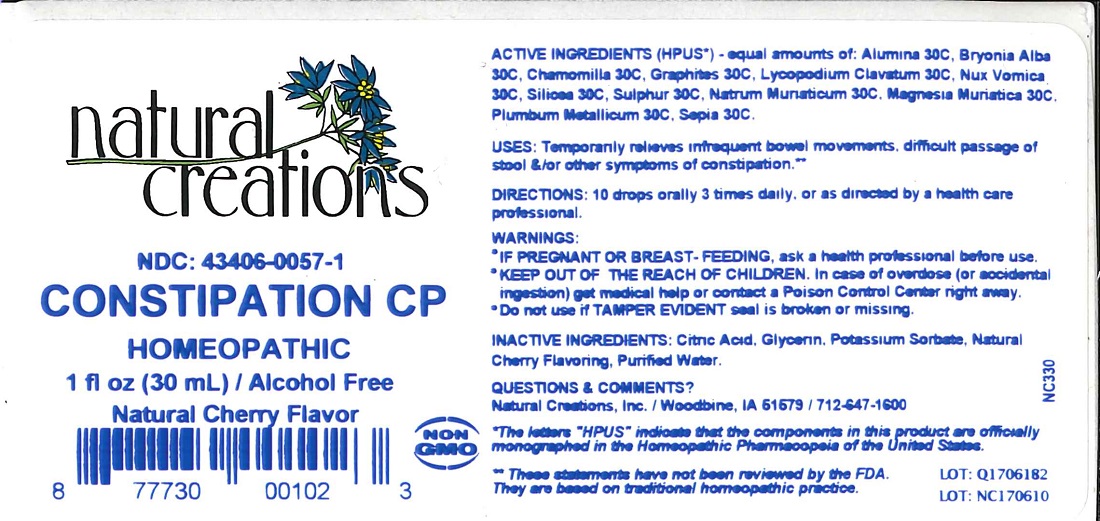 DRUG LABEL: CONSTIPATION CP
NDC: 43406-0057 | Form: LIQUID
Manufacturer: Natural Creations, Inc.
Category: homeopathic | Type: HUMAN OTC DRUG LABEL
Date: 20211115

ACTIVE INGREDIENTS: ALUMINUM OXIDE 30 [hp_C]/1 mL; BRYONIA ALBA ROOT 30 [hp_C]/1 mL; MATRICARIA RECUTITA 30 [hp_C]/1 mL; GRAPHITE 30 [hp_C]/1 mL; LYCOPODIUM CLAVATUM SPORE 30 [hp_C]/1 mL; STRYCHNOS NUX-VOMICA SEED 30 [hp_C]/1 mL; SILICON DIOXIDE 30 [hp_C]/1 mL; SULFUR 30 [hp_C]/1 mL; SODIUM CHLORIDE 30 [hp_C]/1 mL; MAGNESIUM CHLORIDE 30 [hp_C]/1 mL; LEAD 30 [hp_C]/1 mL; SEPIA OFFICINALIS JUICE 30 [hp_C]/1 mL
INACTIVE INGREDIENTS: CITRIC ACID ACETATE; GLYCERIN; POTASSIUM SORBATE; WATER

CONSTIPATION CP

ACTIVE INGREDIENT

ACTIVE INGREDIENTS (HPUS*) - equal amounts of: Alumina 30C, Bryonia Alba 30C, Chamomilla 30C, Graphites 30C, Lycopodium Clavatum 30C, Nux Vomica 30C, Silicea 30C, Sulphur 30C, Natrum Muriaticum 30C, Magnesia Muriatica 30C, Plumbum Metallicum 30C, Sepia 30C.

PURPOSE

USES: Temporarily relieves infrequent bowel movements, difficult passage of stool &/or other symptoms of constipation.**

INDICATIONS AND USAGE

USES: Temporarily relieves infrequent bowel movements, difficult passage of stool &/or other symptoms of constipation.**

DOSAGE AND ADMINISTRATION

DIRECTIONS: 10 drops orally 3 times daily, or as directed by a health care professional.

WARNINGS:

* IF PREGNANT OR BREAST-FEEDING, ask a health care professional before use.

* KEEP OUT OF THE REACH OF CHILDREN. In case of overdose (or accidental ingestion) get medical help or contact a Poison Control Center right away.

* Do not use if TAMPER EVIDENT seal is broken or missing.

KEEP OUT OF REACH OF CHILDREN

KEEP OUT OF THE REACH OF CHILDREN. In case of overdose (or accidental ingestion) get medical help or contact a Poison Control Center right away.

INACTIVE INGREDIENT

INACTIVE INGREDIENTS: Citric Acid, Glycerin, Potassium Sorbate, Purified Water, Natural Cherry Flavor.

QUESTIONS & COMMENTS?

Natural Creations, Inc. / Woodbine, IA 51579 / 712-647-1600

REFERENCES

* The letters "HPUS" indicate the components in the product are officially monographed in the Homeopathic Pharmacopeia of the United States.

** These statements have not been reviewed by the FDA. They are based on traditional homeopathic practice.

LOT:

PACKAGE LABEL

NDC: 43406-0057-1

CONSTIPATION CP

HOMEOPATHIC

1 fl oz (30 mL) / Alcohol Free

Natural Cherry Flavor

UPC: 877730001023